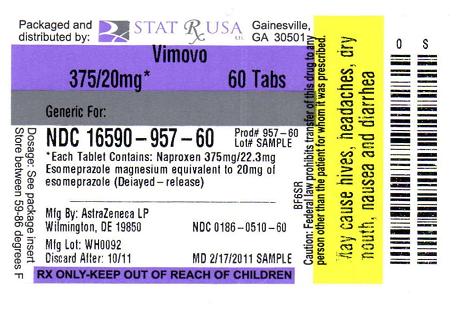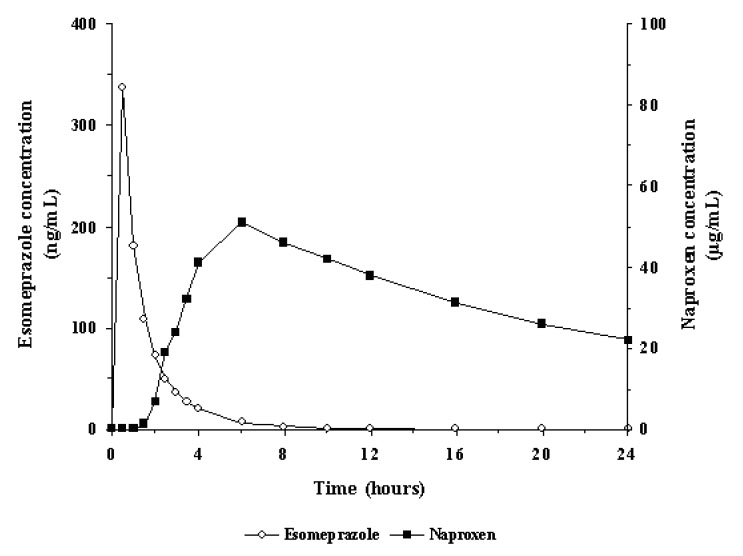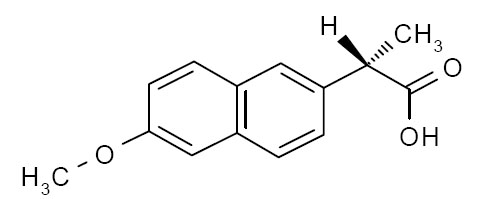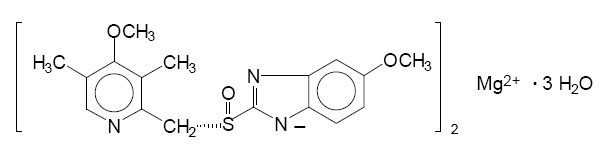 DRUG LABEL: VIMOVO
NDC: 16590-957 | Form: TABLET, DELAYED RELEASE
Manufacturer: STAT RX USA LLC
Category: prescription | Type: HUMAN PRESCRIPTION DRUG LABEL
Date: 20110729

ACTIVE INGREDIENTS: NAPROXEN 375 mg/1 1; ESOMEPRAZOLE MAGNESIUM 20 mg/1 1
INACTIVE INGREDIENTS: CARNAUBA WAX; SILICON DIOXIDE; CROSCARMELLOSE SODIUM; FERRIC OXIDE YELLOW; GLYCERYL MONOSTEARATE; HYPROMELLOSES; MAGNESIUM STEARATE; METHACRYLIC ACID; METHYLPARABEN; POLYSORBATE 80; POLYETHYLENE GLYCOL; POVIDONE; PROPYLENE GLYCOL; PROPYLPARABEN; TITANIUM DIOXIDE; TRIETHYL CITRATE; FERROSOFERRIC OXIDE; POLYDEXTROSE

HIGHLIGHTS OF PRESCRIBING INFORMATION

These highlights do not include all the information needed to use VIMOVO safely and effectively. See full prescribing information for VIMOVO.
VIMOVO®
(naproxen and esomeprazole magnesium) DELAYED RELEASE TABLETS
Initial U.S. Approval: April 2010

Recent Major Changes

WARNINGS AND PRECAUTIONS 05/2011

Hypomagnesemia (5.19)

Concomitant use of St John’s Wort or Rifampin with VIMOVO (5.20) 06/2011

Cardiovascular Risk

WARNING: CARDIOVASCULAR AND GASTROINTESTINAL RISKS

See full prescribing information for complete boxed warning

Cardiovascular Risk

• Naproxen, a component of VIMOVO, may cause an increased risk of serious cardiovascular thrombotic events, myocardial infarction, and stroke, which can be fatal. This risk may increase with duration of use. Patients with cardiovascular disease or risk factors for cardiovascular disease may be at greater risk. (5.1)

• VIMOVO is contraindicated for the treatment of peri-operative pain in the setting of coronary artery bypass graft (CABG) surgery. (4, 5.1)

Gastrointestinal Risk

• NSAIDs, including naproxen, a component of VIMOVO, cause an increased risk of serious gastrointestinal adverse events including bleeding, ulceration, and perforation of the stomach or intestines, which can be fatal. These events can occur at any time during use and without warning symptoms. Elderly patients are at greater risk for serious gastrointestinal (GI) events. (5.4)

1 INDICATIONS AND USAGE

Relief of signs and symptoms of osteoarthritis, rheumatoid arthritis, and ankylosing spondylitis and to decrease the risk of developing gastric ulcers in patients at risk of developing NSAID associated gastric ulcers (1)

2 DOSAGE AND ADMINISTRATION

One tablet twice daily. Use the lowest effective dose. Should be avoided in moderate/severe renal insufficiency or in severe hepatic insufficiency. Consider dose reduction in mild/moderate hepatic insufficiency (2)

3 DOSAGE FORMS AND STRENGTHS

Delayed release tablets: 375 mg/20 mg or 500 mg/20 mg of naproxen and esomeprazole magnesium (3)

4 CONTRAINDICATIONS

• Known hypersensitivity to any component of VIMOVO or substituted benzimidazoles (4)

• History of asthma, urticaria, or other allergic-type reactions after taking aspirin or other NSAIDs (4, 5.8, 5.9, 5.13)

• Use during the peri-operative period in the setting of coronary artery bypass graft (CABG) surgery (4, 5.1)

• Late pregnancy (4, 5.10, 8.1)

5 WARNINGS AND PRECAUTIONS

• Serious and potentially fatal cardiovascular (CV) thrombotic events, myocardial infarction, and stroke. Patients with known CV disease/risk factors may be at greater risk (5.1)

• Serious gastrointestinal (GI) adverse events, which can be fatal. The risk is greater in patients with a prior history of ulcer disease or GI bleeding, and in patients at high risk for GI events, especially the elderly. VIMOVO should be used with caution in these patients (5.4, 8.5)

• Treatment should be withdrawn when active and clinically significant bleeding from any source occurs (5.5)

• Elevated liver enzymes and, rarely, severe hepatic reactions. Discontinue use immediately if abnormal liver enzymes persist or worsen (5.11, 8.6, 12.3)

• Should be avoided in patients with severe hepatic impairment (e.g., Childs-Pugh C)

• New onset or worsening of pre-existing hypertension. Blood pressure should be monitored closely during treatment with VIMOVO (5.2, 7.1, 7.4)

• Congestive heart failure and edema. VIMOVO should be used with caution in patients with fluid retention or heart failure (5.3)

• Renal papillary necrosis and other renal injury with long-term use. Use VIMOVO with caution in the elderly, those with impaired renal function, hypovolemia, salt depletion, heart failure, liver dysfunction, and those taking diuretics, or ACE-inhibitors. Not recommended for patients with moderate or severe renal impairment (2, 5.6, 5.7, 7.1, 7.4, 8.7)

• Anaphylactoid reactions. Do not use VIMOVO in patients with the aspirin triad (5.8)

• Serious skin adverse reactions such as exfoliative dermatitis, Stevens-Johnson syndrome, and toxic epidermal necrolysis, which can be fatal and can occur without warning. Discontinue VIMOVO at first appearance of skin rash or any other sign of hypersensitivity (5.9)

• Long-term PPI therapy is associated with an increased risk for osteoporosis-related fractures of the hip, wrist or spine (5.16)

• Symptomatic response to esomeprazole does not preclude the presence of gastric malignancy (5.4)

• Atrophic gastritis has been noted on biopsy with long-term omeprazole therapy (5.4)

• Interactions with diagnostic investigations for Neuroendocrine Tumors: Increases in intragastric pH may result in hypergastrinemia, enterochromaffin-like cell hyperplasia, and increased Chromogranin A levels which may interfere with diagnostic investigations for neuroendocrine tumors. (5.18)

• Hypomagnesemia has been reported rarely with prolonged treatment with PPIs (5.19)

• Avoid concomitant use of VIMOVO with St John’s Wort or rifampin due to the potential reduction in esomeprazole levels. (5.20, 7.16)

6 ADVERSE REACTIONS

Most common adverse reactions in clinical trials (>5%): erosive gastritis, dyspepsia, gastritis, diarrhea, gastric ulcer, upper abdominal pain, nausea (6.1)

To report SUSPECTED ADVERSE REACTIONS, contact AstraZeneca at 1-800-236-9933 or FDA at 1-800-FDA-1088 or www.fda.gov/medwatch.

7 DRUG INTERACTIONS

• Concomitant use of NSAIDs may reduce the antihypertensive effect of ACE Inhibitors, diuretics, and beta-blockers (7.1, 7.4, 7.9)

• Concomitant use of NSAIDs increases lithium plasma levels (7.5)

• Concomitant use of VIMOVO with methotrexate may increase the toxicity of methotrexate (7.6)

• Concomitant use of VIMOVO with warfarin may result in increased risk of bleeding complications. Monitor for increases in INR and prothrombin time (7.7)

• Esomeprazole inhibits gastric acid secretion and may interfere with the absorption of drugs where gastric pH is an important determinant of bioavailability (eg, ketoconazole, iron salts and digoxin) Patients treated with VIMOVO and digoxin may need to be monitored for increases in digoxin toxicity (7.12)

• As with all NSAIDs caution is advised when cyclosporin is co-administered because of the increased risk of nephrotoxicity. (7.4)

• Tacrolimus: Concomitant administration of esomeprazole, a component of VIMOVO, and tacrolimus may increase the serum levels of tacrolimus. (7.5)

8 USE IN SPECIFIC POPULATIONS

• Pregnancy Category C: VIMOVO should not be used in late pregnancy (4, 5.10, 8.1)

• Hepatic Insufficiency: VIMOVO should be avoided in patients with severe hepatic insufficiency (2, 4, 5.11, 8.6, 12.3)

• Renal Insufficiency: VIMOVO is not recommended in patients with moderate or severe renal insufficiency (2, 5.6, 5.7, 8.7, 12.3)

FULL PRESCRIBING INFORMATION

Cardiovascular Risk

• Non-Steroidal Anti-inflammatory Drugs (NSAIDs), a component of VIMOVO, may cause an increased risk of serious cardiovascular thrombotic events, myocardial infarction, and stroke, which can be fatal. This risk may increase with duration of use. Patients with cardiovascular disease or risk factors for cardiovascular disease may be at greater risk [see Warnings and Precautions (5.1)].

• VIMOVO is contraindicated for the treatment of peri-operative pain in the setting of coronary artery bypass graft (CABG) surgery [see Contraindications (4), and Warnings and Precautions (5.1)].

Gastrointestinal Risk

• NSAIDs, including naproxen, a component of VIMOVO, cause an increased risk of serious gastrointestinal adverse events including bleeding, ulceration, and perforation of the stomach or intestines, which can be fatal. These events can occur at any time during use and without warning symptoms. Elderly patients are at greater risk for serious gastrointestinal events [see Warnings and Precautions (5.4)].

1 INDICATIONS AND USAGE

VIMOVO is a combination product that contains naproxen and esomeprazole. It is indicated for the relief of signs and symptoms of osteoarthritis, rheumatoid arthritis and ankylosing spondylitis and to decrease the risk of developing gastric ulcers in patients at risk of developing NSAID-associated gastric ulcers. VIMOVO is not recommended for initial treatment of acute pain because the absorption of naproxen is delayed compared to absorption from other naproxen-containing products. Controlled studies do not extend beyond 6 months.

2 DOSAGE AND ADMINISTRATION

Carefully consider the potential benefits and risks of VIMOVO and other treatment options before deciding to use VIMOVO. Use the lowest effective dose for the shortest duration consistent with individual patient treatment goals. VIMOVO does not allow for administration of a lower daily dose of esomeprazole. If a dose of esomeprazole lower than a total daily dose of 40 mg is more appropriate, a different treatment should be considered.

Rheumatoid Arthritis, Osteoarthritis and Ankylosing Spondylitis

The dosage is one tablet twice daily of VIMOVO 375 mg naproxen and 20 mg of esomeprazole or 500 mg naproxen and 20 mg of esomeprazole.

The tablets are to be swallowed whole with liquid. Do not split, chew, crush or dissolve the tablet. VIMOVO is to be taken at least 30 minutes before meals.

Geriatric Patients

Studies indicate that although total plasma concentration of naproxen is unchanged, the unbound plasma fraction of naproxen is increased in the elderly. Use caution when high doses are required and some adjustment of dosage may be required in elderly patients. As with other drugs used in the elderly use the lowest effective dose [see Use in Specific Populations (8.5) and Clinical Pharmacology (12.3)].

Patients With Moderate to Severe Renal Impairment

Naproxen-containing products are not recommended for use in patients with moderate to severe or severe renal impairment (creatinine clearance <30 mL/min) [see Warnings and Precautions (5.6, 5.7) and Use in Specific Populations (8.7)].

Hepatic Insufficiency

Monitor patients with mild to moderate hepatic impairment closely and consider a possible dose reduction based on the naproxen component of VIMOVO.

VIMOVO should be avoided in patients with severe hepatic impairment [see Warnings and Precautions (5.11), Use in Specific Populations (8.6) and Clinical Pharmacology (12.3)].

Pediatric Patients

The safety and efficacy of VIMOVO in children younger than 18 years has not been established. VIMOVO is therefore not recommended for use in children.

3 DOSAGE FORMS AND STRENGTHS

Oval, yellow, delayed release tablets for oral administration containing either:

• 375 mg enteric coated naproxen and 20 mg esomeprazole (as magnesium trihydrate) tablets printed with 375/20 in black, or

• 500 mg enteric coated naproxen and 20 mg esomeprazole (as magnesium trihydrate) tablets printed with 500/20 in black.

4 CONTRAINDICATIONS

VIMOVO is contraindicated in patients with known hypersensitivity to naproxen, esomeprazole magnesium, substituted benzimidazoles, or to any of the excipients.

VIMOVO is contraindicated in patients who have experienced asthma, urticaria, or allergic-type reactions after taking aspirin or other NSAIDs. Severe, rarely fatal, anaphylactic-like reactions to NSAIDs have been reported in such patients [see Warnings and Precautions (5.8, 5.13)]. Hypersensitivity reactions, eg, angioedema and anaphylactic reaction/shock, have been reported with esomeprazole use.

VIMOVO is contraindicated for the treatment of peri-operative pain in the setting of coronary artery bypass graft (CABG) surgery [see Warnings and Precautions (5.1)].

VIMOVO is contraindicated in patients in the late stages of pregnancy [see Warnings and Precautions (5.10) and Use in Specific Populations (8.1)].

5 WARNINGS AND PRECAUTIONS

5.1 Cardiovascular Thrombotic Events

Clinical trials of several COX-2 selective and nonselective NSAIDs of up to three years duration have shown an increased risk of serious cardiovascular (CV) thrombotic events, myocardial infarction, and stroke, which can be fatal. All NSAIDS, both COX-2 selective and nonselective, may have a similar risk. Patients with known CV disease or risk factors for CV disease may be at greater risk. To minimize the potential risk for an adverse CV event in patients treated with an NSAID, the lowest effective dose should be used for the shortest duration possible. Physicians and patients should remain alert for the development of such events, even in the absence of previous CV symptoms. Patients should be informed about the signs and/or symptoms of serious CV events and the steps to take if they occur.

There is no consistent evidence that concurrent use of aspirin mitigates the increased risk of serious CV thrombotic events associated with NSAID use.

Two large, controlled, clinical trials of a COX-2 selective NSAID for the treatment of pain in the first 10–14 days following CABG surgery found an increased incidence of myocardial infarction and stroke [see Contraindications (4)].

5.2 Hypertension

NSAIDs, including naproxen, a component of VIMOVO, can lead to onset of new hypertension or worsening of pre-existing hypertension, either of which may contribute to the increased incidence of CV events. Patients taking thiazides or loop diuretics may have impaired response to these therapies when taking NSAIDs. NSAIDs should be used with caution in patients with hypertension. Blood pressure (BP) should be monitored closely during the initiation of NSAID treatment and throughout the course of therapy [see Drug Interactions (7.1, 7.4)].

5.3 Congestive Heart Failure and Edema

Fluid retention, edema, and peripheral edema have been observed in some patients taking NSAIDs and should be used with caution in patients with fluid retention or heart failure.

5.4 Gastrointestinal Effects — Risk of Ulceration, Bleeding, and Perforation

NSAIDs, including naproxen, a component of VIMOVO, can cause serious gastrointestinal (GI) adverse events including inflammation, bleeding, ulceration, and perforation of the stomach, small intestine, or large intestine, which can be fatal. While VIMOVO has been shown to significantly decrease the occurrence of gastric ulcers compared to naproxen alone, ulceration and associated complications can still occur.

These serious adverse events can occur at any time, with or without warning symptoms, in patients treated with NSAIDs. Only one in five patients who develop a serious upper GI adverse event on NSAID therapy is symptomatic. Upper GI ulcers, gross bleeding, or perforation caused by NSAIDs occur in approximately 1% of patients treated for 3–6 months, and in about 2–4% of patients treated for one year. These trends continue with longer duration of use, increasing the likelihood of developing a serious GI event at some time during the course of therapy. However, even short-term therapy is not without risk. The utility of periodic laboratory monitoring has not been demonstrated, nor has it been adequately assessed.

VIMOVO should be prescribed with caution in those with a prior history of ulcer disease or gastrointestinal bleeding. Patients with a prior history of peptic ulcer disease and/or gastrointestinal bleeding who use NSAIDs have a greater than 10-fold increased risk of developing a GI bleed compared to patients with neither of these risk factors. Other factors that increase the risk for GI bleeding in patients treated with NSAIDs include concomitant use of oral corticosteroids or anticoagulants or antiplatelets (including low-dose aspirin), longer duration of NSAID therapy, smoking, use of alcohol, older age, and poor general health status. Most spontaneous reports of fatal GI events are in elderly or debilitated patients, and therefore special care should be taken in treating this population.

To minimize the potential risk for an adverse GI event in patients treated with an NSAID or NSAID-containing product, the lowest effective dose should be used for the shortest possible duration. Patients and physicians should remain alert for signs and symptoms of GI ulceration and bleeding during NSAID therapy and promptly initiate additional evaluation and treatment if a serious GI adverse event is suspected. This should include discontinuation of the NSAID until a serious GI adverse event is ruled out. For high risk patients, alternate therapies that do not involve NSAIDs should be considered.

Epidemiological studies of the case-control and cohort design have demonstrated an association between use of psychotropic drugs that interfere with serotonin reuptake and the occurrence of upper gastrointestinal bleeding. In two studies, concurrent use of an NSAID, COX-2 inhibitor, or aspirin potentiated the risk of bleeding [see Drug Interactions (7.2, 7.8)]. Although these studies focused on upper gastrointestinal bleeding, bleeding at other sites cannot be ruled out.

NSAIDs should be given with care to patients with a history of inflammatory bowel disease (ulcerative colitis, Crohn’s disease) as their condition may be exacerbated.

Gastrointestinal symptomatic response to therapy with VIMOVO does not preclude the presence of gastric malignancy.

Atrophic gastritis has been noted occasionally in gastric corpus biopsies from patients treated long-term with omeprazole, of which esomeprazole is an enantiomer and a component of VIMOVO.

5.5 Active Bleeding

When active and clinically significant bleeding from any source occurs in patients receiving VIMOVO, the treatment should be withdrawn.

5.6 Renal Effects

Long-term administration of NSAIDs has resulted in renal papillary necrosis and other renal injury. Renal toxicity has also been seen in patients in whom renal prostaglandins have a compensatory role in the maintenance of renal perfusion. In these patients, administration of an NSAID may cause a dose-dependent reduction in prostaglandin formation and, secondarily, in renal blood flow, which may precipitate overt renal decompensation. Patients at greatest risk of this reaction are those with impaired renal function, hypovolemia, heart failure, liver dysfunction, salt depletion, those taking diuretics and ACE inhibitors, and the elderly. Discontinuation of NSAID therapy is usually followed by recovery to the pretreatment state.

5.7 Advanced Renal Disease

No information is available from controlled clinical studies regarding the use of VIMOVO in patients with advanced renal disease. Therefore, treatment with VIMOVO is not recommended in these patients with advanced renal disease. If VIMOVO therapy must be initiated, close monitoring of the patient’s renal function is advisable [see Dosage and Administration (2), Use in Specific Populations (8.7) and Clinical Pharmacology (12.3)].

5.8 Anaphylactoid Reactions

Anaphylactoid reactions may occur in patients without known prior exposure to either component of VIMOVO. NSAIDs should not be given to patients with the aspirin triad. This symptom complex typically occurs in asthmatic patients who experience rhinitis with or without nasal polyps, or who exhibit severe, potentially fatal bronchospasm after taking aspirin or other NSAIDs [see Contraindications (4)]. Emergency help should be sought in cases where an anaphylactoid reaction occurs. Anaphylactoid reactions, like anaphylaxis, may have a fatal outcome.

5.9 Skin Reactions

NSAIDs can cause serious skin adverse events such as exfoliative dermatitis, Stevens-Johnson syndrome, and toxic epidermal necrolysis, which can be fatal. These serious events may occur without warning. Patients should be informed about the signs and symptoms of serious skin manifestations and use of the drug should be discontinued at the first appearance of skin rash or any other sign of hypersensitivity.

5.10 Pregnancy

Pregnancy Category C

In late pregnancy, as with other NSAIDs, naproxen, a component of VIMOVO, should be avoided because it may cause premature closure of the ductus arteriosus [see Contraindications (4), and Use in Specific Populations (8.1)].

5.11 Hepatic Effects

Borderline elevations of one or more liver tests may occur in up to 15% of patients taking NSAIDs including naproxen, a component of VIMOVO. Hepatic abnormalities may be the result of hypersensitivity rather than direct toxicity. These laboratory abnormalities may progress, may remain essentially unchanged, or may be transient with continued therapy. The SGPT (ALT) test is probably the most sensitive indicator of liver dysfunction. Notable elevations of ALT or AST (approximately three or more times the upper limit of normal) have been reported in approximately 1% of patients in clinical trials with NSAIDs. In addition, rare cases of severe hepatic reactions, including jaundice and fatal fulminant hepatitis, liver necrosis and hepatic failure, some of them with fatal outcomes, have been reported.

A patient with symptoms and/or signs suggesting liver dysfunction, or in whom an abnormal liver test has occurred, should be evaluated for evidence of the development of more severe hepatic reaction while on therapy with VIMOVO.

If clinical signs and symptoms consistent with liver disease develop, or if systemic manifestations occur (eg, eosinophilia, rash, etc.), VIMOVO should be discontinued.

Chronic alcoholic liver disease and probably other diseases with decreased or abnormal plasma proteins (albumin) reduce the total plasma concentration of naproxen, but the plasma concentration of unbound naproxen is increased. Caution is advised when high doses are required and some adjustment of dosage may be required in these patients. It is prudent to use the lowest effective dose for the shortest possible duration of adequate treatment.

VIMOVO should be avoided in patients with severe hepatic impairment [see Dosage and Administration (2), Use in Specific Populations (8.6), and Clinical Pharmacology (12.3)].

5.12 Hematological Effects

Anemia is sometimes seen in patients receiving NSAIDs. This may be due to fluid retention, occult or gross GI blood loss, or an incompletely described effect upon erythropoiesis. Patients on long-term treatment with NSAIDs should have their hemoglobin or hematocrit checked if they exhibit any signs or symptoms of anemia.

NSAIDs inhibit platelet aggregation and have been shown to prolong bleeding time in some patients. Unlike aspirin, their effect on platelet function is quantitatively less, of shorter duration, and reversible. Patients receiving VIMOVO who may be adversely affected by alterations in platelet function, such as those with coagulation disorders or patients receiving anticoagulants or antiplatelets, should be carefully monitored.

5.13 Pre-existing Asthma

Patients with asthma may have aspirin-sensitive asthma. The use of aspirin in patients with aspirin-sensitive asthma has been associated with severe bronchospasm, which can be fatal. Since cross reactivity, including bronchospasm, between aspirin and other NSAIDs has been reported in such aspirin-sensitive patients, VIMOVO should not be administered to patients with this form of aspirin sensitivity and should be used with caution in patients with pre-existing asthma.

5.14 Concomitant NSAID Use

VIMOVO contains naproxen as one of its active ingredients. It should not be used with other naproxen-containing products since they all circulate in the plasma as the naproxen anion.

The concomitant use of VIMOVO with any dose of a non-aspirin NSAID should be avoided due to the potential for increased risk of adverse reactions.

5.15 Corticosteroid Treatment

VIMOVO cannot be expected to substitute for corticosteroids or to treat corticosteroid insufficiency. Abrupt discontinuation of corticosteroids may lead to disease exacerbation. Patients on prolonged corticosteroid therapy should have their therapy tapered slowly if a decision is made to discontinue corticosteroids and the patient should be observed closely for any evidence of adverse effects, including adrenal insufficiency and exacerbation of symptoms of arthritis.

5.16 Bone Fracture

Several studies and literature reports indicate that proton pump inhibitor (PPI) therapy is associated with an increased risk for osteoporosis-related fractures of the hip, wrist, or spine. Those patients with the highest risk received high-dose or long-term PPI therapy (a year or longer). Patients should use the lowest effective dose and shortest duration of PPI therapy appropriate to the condition being treated. Patients at risk for osteoporosis-related fractures should be managed according to the established treatment guidelines. Adequate vitamin D and calcium intake is recommended.

5.17 Masking of Inflammation and Fever

The pharmacological activity of VIMOVO in reducing fever and inflammation may diminish the utility of these diagnostic signs in detecting complications of presumed noninfectious, noninflammatory painful conditions.

5.18 Laboratory Tests

Because serious GI tract ulcerations and bleeding can occur without warning symptoms, physicians should monitor for signs or symptoms of GI bleeding. Patients on long-term treatment with NSAIDs should have their CBC and a chemistry profile checked periodically. If clinical signs and symptoms consistent with liver or renal disease develop, systemic manifestations occur (eg, eosinophilia, rash, etc.) or if abnormal liver tests persist or worsen, VIMOVO should be discontinued.

Patients with initial hemoglobin values of 10 g or less who are to receive long-term therapy should have hemoglobin values determined periodically.

Serum chromogranin A (CgA) levels increase secondary to drug-induced decreases in gastric acidity. The increased CgA level may cause false positive results in diagnostic investigations for neuroendocrine tumors. Providers should temporarily stop esomeprazole treatment before assessing CgA levels and consider repeating the test if initial CgA levels are high. If serial tests are performed (e.g. for monitoring), the same commercial laboratory should be used for testing, as reference ranges between tests may vary [see Pharmacodynamics (12.2)].

5.19 Hypomagnesemia

Hypomagnesemia, symptomatic and asymptomatic, has been reported rarely in patients treated with PPIs for at least three months, in most cases after a year of therapy. Serious adverse events include tetany, arrhythmias, and seizures. In most patients, treatment of hypomagnesemia required magnesium replacement and discontinuation of the PPI.

For patients expected to be on prolonged treatment or who take PPIs with medications such as digoxin or drugs that may cause hypomagnesemia (e.g., diuretics), health care professionals may consider monitoring magnesium levels prior to initiation of PPI treatment and periodically. [see Adverse Reactions (6.2)]

5.20 Concomitant use of St John's Wort or Rifampin with VIMOVO

Drugs that induce CYP2C19 or CYP3A4 (such as St John’s Wort or rifampin) can substantially decrease esomeprazole concentrations. Avoid concomitant use of VIMOVO with St John’s Wort or rifampin [see Drug Interactions (7.15)].

6 ADVERSE REACTIONS

6.1 Clinical Trials Experience

Because clinical trials are conducted under widely varying conditions, adverse reaction rates observed in the clinical trials of a drug cannot be directly compared to rates in the clinical trials of another drug and may not reflect the rates observed in practice.

The adverse reactions reported below are specific to the clinical trials with VIMOVO. See also the full prescribing information for naproxen and esomeprazole magnesium products.

The safety of VIMOVO was evaluated in clinical studies involving 2317 patients (aged 27 to 90 years) and ranging from 3-12 months. Patients received either 500 mg/20 mg of VIMOVO twice daily (n=1157), 500 mg of enteric-coated naproxen twice daily (n=426), or placebo (n=246). The average number of VIMOVO doses taken over 12 months was 696+44.

The table below lists all adverse reactions, regardless of causality, occurring in >2% of patients receiving VIMOVO from two clinical studies (Study 1 and Study 2). Both of these studies were randomized, multi-center, double-blind, parallel studies. The majority of patients were female (67%), white (86%). The majority of patients were 50-69 years of age (83%). Approximately one quarter were on low-dose aspirin.

Table 1: Adverse Reactions occurring in patients >2% Study 1 and Study 2 (endoscopic studies)
Preferred term (sorted by SOC) | VIMOVO 500 mg/20 mg twice daily; (n=428); % | EC-Naproxen 500 mg twice daily; (n=426); %
Gastrointestinal Disorders
Gastritis Erosive | 19 | 38
Dyspepsia | 18 | 27
Gastritis | 17 | 14
Diarrhea | 6 | 5
Gastric Ulcer | 6 | 24
Abdominal Pain Upper | 6 | 9
Nausea | 5 | 5
Hiatus Hernia | 4 | 6
Abdominal Distension | 4 | 4
Flatulence | 4 | 3
Esophagitis | 4 | 8
Constipation | 3 | 3
Abdominal pain | 2 | 2
Erosive Duodenitis | 2 | 12
Abdominal pain lower | 2 | 3
Duodenitis | 1 | 7
Gastritis hemorrhagic | 1 | 2
Gastroesophageal reflux disease | <1 | 4
Duodenal ulcer | <1 | 5
Erosive esophagitis | <1 | 6
Infections and infestations
Upper respiratory tract infection | 5 | 4
Bronchitis | 2 | 2
Urinary tract infection | 2 | 1
Sinusitis | 2 | 2
Nasopharyngitis | <1 | 2
Musculoskeletal and connective tissue disorders
Arthralgia | 1 | 2
Nervous system disorders
Headache | 3 | 1
Dysgeusia | 2 | 1
Respiratory, thoracic and mediastinal disorders
Cough | 2 | 3

In Study 1 and Study 2, patients taking VIMOVO had fewer premature discontinuations due to adverse reactions compared to patients taking enteric-coated naproxen alone (7.9% vs. 12.5% respectively). The most common reasons for discontinuations due to adverse events in the VIMOVO treatment group were upper abdominal pain (1.2%, n=5), duodenal ulcer (0.7%, n=3) and erosive gastritis (0.7%, n=3). Among patients receiving enteric-coated naproxen, the most common reasons for discontinuations due to adverse events were duodenal ulcer 5.4% (n=23), dyspepsia 2.8% (n=12) and upper abdominal pain 1.2% (n=5). The proportion of patients discontinuing treatment due to any upper gastrointestinal adverse events (including duodenal ulcers) in patients treated with VIMOVO was 4% compared to 12% for patients taking enteric-coated naproxen.

The table below lists all adverse reactions, regardless of causality, occurring in >2% of patients from 2 clinical studies conducted in patients with osteoarthritis of the knee (Study 3 and Study 4).

Table 2: Adverse Reactions occurring in patients >2% (Study 3 and Study 4)
Preferred term (sorted by SOC) | VIMOVO 500 mg/20 mg twice daily; (n=490); % | Placebo; (n=246); %
Gastrointestinal Disorders
Dyspepsia | 8 | 12
Diarrhea | 6 | 4
Abdominal Pain Upper | 4 | 3
Constipation | 4 | 1
Nausea | 4 | 4
Nervous System Disorders
Dizziness | 3 | 2
Headache | 3 | 5
General disorders and administration site conditions
Peripheral edema | 3 | 1
Respiratory, thoracic and mediastinal disorders
Cough | 1 | 3
Infections and infestations
Sinusitis | 1 | 2

The percentage of subjects who withdrew from the VIMOVO treatment group in these studies due to treatment-emergent adverse events was 7%. There were no preferred terms in which more than 1% of subjects withdrew from any treatment group.

The long-term safety of VIMOVO was evaluated in an open-label clinical trial of 239 patients, of which 135 patients received 500 mg/20 mg of VIMOVO for 12 months. There were no differences in frequency or types of adverse reactions seen in the long-term safety study compared to shorter-term treatment in the randomized controlled studies.

6.2 Postmarketing Experience

Naproxen

The following adverse reactions have been identified during post-approval use of naproxen. Because these reactions are reported voluntarily from a population of uncertain size, it is not always possible to reliably estimate their frequency or establish a causal relationship to drug exposure. These reports are listed below by body system:

Body as a Whole: anaphylactoid reactions, angioneurotic edema, menstrual disorders, pyrexia (chills and fever)

Cardiovascular: congestive heart failure, vasculitis, hypertension, pulmonary edema

Gastrointestinal: gastrointestinal bleeding and/or perforation, hematemesis, pancreatitis, vomiting, colitis, exacerbation of inflammatory bowel disease (ulcerative colitis, Crohn’s disease), nonpeptic gastrointestinal ulceration, ulcerative stomatitis, esophagitis, peptic ulceration

Hepatobiliary: jaundice, abnormal liver function tests, hepatitis (some cases have been fatal)

Hemic and Lymphatic: eosinophilia, leukopenia, melena, thrombocytopenia, agranulocytosis, granulocytopenia, hemolytic anemia, aplastic anemia

Metabolic and Nutritional: hyperglycemia, hypoglycemia

Nervous System: inability to concentrate, depression, dream abnormalities, insomnia, malaise, myalgia, muscle weakness, aseptic meningitis, cognitive dysfunction, convulsions

Respiratory: eosinophilic pneumonitis, asthma

Dermatologic: alopecia, urticaria, skin rashes, toxic epidermal necrolysis, erythema multiforme, erythema nodosum, fixed drug eruption, lichen planus, pustular reaction, systemic lupus erythematoses, bullous reactions, including Stevens-Johnson syndrome, photosensitive dermatitis, photosensitivity reactions, including rare cases resembling porphyria cutanea tarda (pseudoporphyria) or epidermolysis bullosa. If skin fragility, blistering or other symptoms suggestive of pseudoporphyria occur, treatment should be discontinued and the patient monitored.

Special Senses: hearing impairment, corneal opacity, papillitis, retrobulbar optic neuritis, papilledema

Urogenital: glomerular nephritis, hematuria, hyperkalemia, interstitial nephritis, nephrotic syndrome, renal disease, renal failure, renal papillary necrosis, raised serum creatinine

Reproduction (female): infertility

Esomeprazole

The following adverse reactions have been identified during post-approval use of esomeprazole. Because these reactions are reported voluntarily from a population of uncertain size, it is not always possible to reliably estimate their frequency or establish a causal relationship to drug exposure. These reports are listed below by body system:

Blood and Lymphatic: agranulocytosis, pancytopenia;

Eye: blurred vision;

Gastrointestinal: pancreatitis; stomatitis;

Hepatobiliary: hepatic failure, hepatitis with or without jaundice;

Immune System: anaphylactic reaction/shock;

Infections and Infestations: GI candidiasis;

Metabolism and Nutritional Disorders: hypomagnesemia

Musculoskeletal and Connective Tissue: muscular weakness, myalgia;

Nervous System: hepatic encephalopathy, taste disturbance;

Psychiatric: aggression, agitation, depression, hallucination;

Renal and Urinary: interstitial nephritis;

Reproductive System and Breast: gynecomastia;

Respiratory, Thoracic, and Mediastinal: bronchospasm;

Skin and Subcutaneous Tissue: alopecia, erythema multiforme, hyperhidrosis, photosensitivity, Stevens-Johnson syndrome, toxic epidermal necrolysis (some fatal).

7 DRUG INTERACTIONS

Several studies conducted with VIMOVO have shown no interaction between the two components, naproxen and esomeprazole.

7.1 ACE-inhibitors

Reports suggest that NSAIDs may diminish the antihypertensive effect of ACE-inhibitors. This interaction should be given consideration in patients taking VIMOVO concomitantly with ACE-inhibitors.

7.2 Aspirin

VIMOVO can be administered with low-dose aspirin (≤325 mg/day) therapy. The concurrent use of aspirin and VIMOVO may increase the risk of serious adverse events [see Warnings and Precautions (5.1, 5.4), Adverse Reactions (6), and Clinical Studies (14)].

When naproxen is administered with doses of aspirin (>1 gram/day), its protein binding is reduced. The clinical significance of this interaction is not known. However, as with other NSAIDs, concomitant administration of naproxen and aspirin is not generally recommended because of the potential of increased adverse effects.

7.3 Cholestyramine

As with other NSAIDs, concomitant administration of cholestyramine can delay the absorption of naproxen.

7.4 Cyclosporin

As with all NSAIDs caution is advised when cyclosporin is co-administered because of the increased risk of nephrotoxicity.

7.5 Tacrolimus

Concomitant administration of esomeprazole, a component of VIMOVO, and tacrolimus may increase the serum levels of tacrolimus.

7.6 Diuretics

Clinical studies, as well as postmarketing observations, have shown that NSAIDs can reduce the natriuretic effect of furosemide and thiazides in some patients. This response has been attributed to inhibition of renal prostaglandin synthesis. During concomitant therapy with NSAIDs, the patient should be observed closely both for signs of renal failure, as well as to monitor to assure diuretic efficacy [see Warnings and Precautions (5.6, 5.7)].

7.7 Lithium

NSAIDs have produced an elevation of plasma lithium levels and a reduction in renal lithium clearance. The mean minimum lithium concentration increased 15% and the renal clearance was decreased by approximately 20%. These effects have been attributed to inhibition of renal prostaglandin synthesis by the NSAID. Thus, when NSAIDs and lithium are administered concurrently, subjects should be observed carefully for signs of lithium toxicity.

7.8 Methotrexate

NSAIDs have been reported to competitively inhibit methotrexate accumulation in rabbit kidney slices. NSAIDs have been reported to reduce the tubular secretion of methotrexate in an animal model. This may indicate that they could enhance the toxicity of methotrexate. Caution should be used when NSAIDs are administered concomitantly with methotrexate.

7.9 Anticoagulants

Naproxen decreases platelet aggregation and may prolong bleeding time. In addition, because warfarin and NSAIDs are highly protein bound, the free fraction of warfarin and naproxen may increase substantially in some patients.

Concomitant use of VIMOVO and anticoagulants (such as warfarin, dicumarol and heparin) may result in increased risk of bleeding complications.

The effects of warfarin and NSAIDs on GI bleeding are synergistic, such that users of both drugs together have a risk of serious GI bleeding higher than users of either drug alone.

Post-marketing reports of changes in prothrombin measures have been reported among patients on concomitant warfarin and esomeprazole therapy. Increases in INR and prothrombin time may lead to abnormal bleeding and even death. Patients treated with proton pump inhibitors and warfarin concomitantly may need to be monitored for increases in INR and prothrombin time.

7.10 Selective Serotonin Reuptake Inhibitors (SSRIs)

There is an increased risk of gastrointestinal bleeding when selective serotonin reuptake inhibitors (SSRIs) are combined with NSAIDs including COX-2 selective inhibitors. Caution should be used when NSAIDs are administered concomitantly with SSRIs [see Warnings and Precautions (5.4)].

7.11 Other Information Concerning Drug Interactions

Naproxen is highly bound to plasma albumin; it thus has a theoretical potential for interaction with other albumin-bound drugs such as sulphonylureas, hydantoins, and other NSAIDs. Patients simultaneously receiving VIMOVO and a hydantoin, sulphonamide or sulphonylurea should be observed for adjustment of dose if required.

Naproxen and other NSAIDs can reduce the antihypertensive effect of propranolol and other beta-blockers.

Probenecid given concurrently increases naproxen anion plasma levels and extends its plasma half-life significantly.

7.12 Interactions With Investigations of Neuroendocrine Tumors

Drug-induced decrease in gastric acidity results in enterochromaffin-like cell hyperplasia and increased Chromogranin A levels which may interfere with investigations for neuroendocrine tumors [see Warnings and Precautions (5.18) and Pharmacodynamics (12.2)].

7.13 Drug/Laboratory Test Interaction

Naproxen may decrease platelet aggregation and prolong bleeding time. This effect should be kept in mind when bleeding times are determined.

The administration of naproxen may result in increased urinary values for 17-ketogenic steroids because of an interaction between the drug and/or its metabolites with m-di-nitrobenzene used in this assay. Although 17-hydroxy-corticosteroid measurements (Porter-Silber test) do not appear to be artifactually altered, it is suggested that therapy with naproxen be temporarily discontinued 72 hours before adrenal function tests are performed if the Porter-Silber test is to be used.

Naproxen may interfere with some urinary assays of 5-hydroxy indoleacetic acid (5HIAA).

7.14 Interactions Related to Absorption

Esomeprazole inhibits gastric acid secretion. Therefore, esomeprazole may interfere with the absorption of drugs where gastric pH is an important determinant of bioavailability (eg, ketoconazole, iron salts and digoxin). Concomitant treatment with omeprazole (20 mg daily) and digoxin in healthy subjects increased the bioavailability of digoxin by 10% (30% in two subjects). Esomeprazole is an enantiomer of omeprazole. Coadministration of digoxin with esomeprazole is expected to increase the systemic exposure of digoxin. Therefore, patients may need to be monitored for increases in digoxin toxicity when digoxin is taken concomitantly with esomeprazole.

7.15 Antiretroviral Agents

Concomitant use of atazanavir and nelfinavir with proton pump inhibitors such as esomeprazole is not recommended. Co-administration of atazanavir with proton pump inhibitors is expected to substantially decrease atazanavir plasma concentrations and thereby reduce its therapeutic effect.

Omeprazole, the racemate of esomeprazole, has been reported to interact with some antiretroviral drugs. The clinical importance and the mechanisms behind these interactions are not always known. Increased gastric pH during omeprazole treatment may change the absorption of the antiretroviral drug. Other possible interaction mechanisms are via CYP2C19. For some antiretroviral drugs, such as atazanavir and nelfinavir, decreased serum levels have been reported when given together with omeprazole. Following multiple doses of nelfinavir (1250 mg, twice daily) and omeprazole (40 mg once a day), AUC was decreased by 36% and 92%, Cmax by 37% and 89% and Cmin by 39% and 75% respectively for nelfinavir and main oxidative metabolite, hydroxy-t-butylamide (M8). Following multiple doses of atazanavir (400 mg, once a day) and omeprazole (40 mg, once a day, 2 hr before atazanavir), AUC was decreased by 94%, Cmax by 96%, and Cmin by 95%. Concomitant administration with omeprazole and drugs such as atazanavir and nelfinavir is therefore not recommended. For other antiretroviral drugs, such as saquinavir, elevated serum levels have been reported with an increase in AUC by 82% in Cmax by 75% and in Cmin by 106% following multiple dosing of saquinavir/ritonavir (1000/100 mg) twice a day for 15 days with omeprazole 40 mg once a day co-administered on days 11 to 15. Therefore, clinical and laboratory monitoring for saquinavir toxicity is recommended during concurrent use with esomeprazole. Dose reduction of saquinavir should be considered from the safety perspective for individual patients. There are also some antiretroviral drugs of which unchanged serum levels have been reported when given with omeprazole.

7.16 Effects on Hepatic Metabolism/Cytochrome P-450 pathways

Esomeprazole is extensively metabolized in the liver by CYP2C19 and CYP3A4.

In vitro and in vivo studies have shown that esomeprazole is not likely to inhibit CYPs 1A2, 2A6, 2C9, 2D6, 2E1 and 3A4. No clinically relevant interactions with drugs metabolized by these CYP enzymes would be expected. Drug interaction studies have shown that esomeprazole does not have any clinically significant interactions with phenytoin, warfarin, quinidine, clarithromycin or amoxicillin.

However, post-marketing reports of changes in prothrombin measures have been received among patients on concomitant warfarin and esomeprazole therapy. Increases in INR and prothrombin time may lead to abnormal bleeding and even death. Patients treated with proton pump inhibitors and warfarin concomitantly may need to be monitored for increases in INR and prothrombin time.

Esomeprazole may potentially interfere with CYP2C19, the major esomeprazole metabolizing enzyme. Co-administration of esomeprazole 30 mg and diazepam, a CYP2C19 substrate, resulted in a 45% decrease in clearance of diazepam.

Concomitant administration of esomeprazole and a combined inhibitor of CYP2C19 and CYP3A4, such as voriconazole, may result in more than doubling of the esomeprazole exposure. Dose adjustment of esomeprazole is not normally required. Omeprazole acts as an inhibitor of CYP2C19. Omeprazole, given in doses of 40 mg daily for one week to 20 healthy subjects in cross-over study, increased Cmax and AUC of cilostazol by 18% and 26% respectively. Cmax and AUC of one of its active metabolites, 3,4-dihydrocilostazol, which has 4-7 times the activity of cilostazol, were increased by 29% and 69% respectively. Co-administration of cilostazol with esomeprazole is expected to increase concentrations of cilostazol and its above mentioned active metabolite. Therefore a dose reduction of cilostazol from 100 mg twice daily to 50 mg twice daily should be considered.

Drugs known to induce CYP2C19 or CYP3A4 (such as rifampin) may lead to decreased esomeprazole serum levels. Omeprazole, of which esomeprazole is an enantiomer, has been reported to interact with St. John’s Wort, an inducer of CYP3A4. In a cross-over study in 12 healthy male subjects, St John’s Wort (300 mg three times daily for 14 days) significantly decreased the systemic exposure of omeprazole in CYP2C19 poor metabolizers (Cmax and AUC decreased by 37.5% and 37.9%, respectively) and extensive metabolizers (Cmax and AUC decreased by 49.6% and 43.9%, respectively). Avoid concomitant use of St. John’s Wort or rifampin with VIMOVO.

7.17 Other Pharmacokinetic-based Interactions

Co-administration of oral contraceptives, diazepam, phenytoin, or quinidine does not seem to change the pharmacokinetic profile of esomeprazole.

8 USE IN SPECIFIC POPULATIONS

8.1 Pregnancy

Teratogenic Effects: Pregnancy Category C prior to 30 weeks gestation; Category D starting 30 weeks gestation.

Starting at 30 weeks gestation, VIMOVO, and other NSAIDs, should be avoided by pregnant women as premature closure of the ductus arteriosus in the fetus may occur. VIMOVO can cause fetal harm when administered to a pregnant woman starting at 30 weeks gestation. If this drug is used during this time period in pregnancy, the patient should be apprised of the potential hazard to a fetus. There are no adequate and well-controlled studies in pregnant women. Prior to 30 weeks gestation, VIMOVO should be used during pregnancy only if the potential benefit justifies the potential risk to the fetus.

Reproductive studies with naproxen have been performed in rats at 20 mg/kg/day (125 mg/m^2/day, 0.23 times the human systemic exposure), rabbits at 20 mg/kg/day (220 mg/m^2/day, 0.27 times the human systemic exposure), and mice at 170 mg/kg/day (510 mg/m^2/day, 0.28 times the human systemic exposure) with no evidence of impaired fertility or harm to the fetus due to the drug [see Animal Toxicology and/or Pharmacology (13.2)]. However, animal reproduction studies are not always predictive of human response.

Reproductive studies in rats and rabbits with esomeprazole and multiple cohort studies in pregnant women with omeprazole use during the first trimester do not show an increased risk of congenital anomalies or adverse pregnancy outcomes. There are no adequate and well controlled studies of esomeprazole use in pregnancy. Because animal reproduction studies are not always predictive of human response, this drug should be used during pregnancy only if clearly needed.

Esomeprazole is the S-isomer of omeprazole. In four population-based cohort studies that included 1226 women exposed during the first trimester of pregnancy to omeprazole there was no increased risk of congenital anomalies.

Reproductive studies with esomeprazole have been performed in rats at doses up to 57 times the human dose and in rabbits at doses up to 35 times the human dose and have revealed no evidence of impaired fertility or harm to the fetus [see Animal Toxicology and/or Pharmacology (13.2)].

Reproductive studies conducted with omeprazole on rats at oral doses up to 56 times the human dose and in rabbits at doses up to 56 times the human dose did not show any evidence of teratogenicity. In pregnant rabbits, omeprazole at doses about 5.5 to 56 times the human dose produced dose-related increases in embryo-lethality, fetal resorptions, and pregnancy loss. In rats treated with omeprazole at doses about 5.6 to 56 times the human dose, dose-related embryo/fetal toxicity and postnatal developmental toxicity occurred in offspring.

8.2 Labor and Delivery

In rat studies with NSAIDs, as with other drugs known to inhibit prostaglandin synthesis, an increased incidence of dystocia, delayed parturition, and decreased pup survival occurred. Naproxen-containing products are not recommended in labor and delivery because, through its prostaglandin synthesis inhibitory effect, naproxen may adversely affect fetal circulation and inhibit uterine contractions, thus increasing the risk of uterine hemorrhage. The effects of VIMOVO on labor and delivery in pregnant women are unknown.

8.3 Nursing Mothers

VIMOVO should not be used in nursing mothers due to the naproxen component.

Naproxen

The naproxen anion has been found in the milk of lactating women at a concentration equivalent to approximately 1% of maximum naproxen concentration in plasma. Because of the possible adverse effects of prostaglandin-inhibiting drugs on neonates, use in nursing mothers should be avoided.

Esomeprazole

The excretion of esomeprazole in milk has not been studied. It is not known whether this drug is excreted in human milk. However, omeprazole concentrations have been measured in breast milk of one woman taking omeprazole 20 mg per day. Because many drugs are excreted in human milk and because of the potential for tumorigenicity shown for esomeprazole in rat carcinogenicity studies, a decision should be made whether to discontinue nursing or to discontinue the drug, taking into account the importance of the drug to the mother.

8.4 Pediatric Use

The safety and efficacy of VIMOVO has not been established in children younger than 18 years.

8.5 Geriatric Use

Of the total number of patients who received VIMOVO (n=1157) in clinical trials, 387 were ≥65 years of age, of which 85 patients were 75 years and over. No meaningful differences in efficacy or safety were observed between these subjects and younger subjects [see Adverse Reactions (6)].

Studies indicate that although total plasma concentration of naproxen is unchanged, the unbound plasma fraction of naproxen is increased in the elderly. Caution is advised when high doses are required and some adjustment of dosage may be required in elderly patients. As with other drugs used in the elderly, it is prudent to use the lowest effective dose [see Dosage and Administration (2) and Clinical Pharmacology (12.3)].

Experience indicates that geriatric patients may be particularly sensitive to certain adverse effects of NSAIDs. Elderly or debilitated patients seem to tolerate peptic ulceration or bleeding less well when these events do occur. Most spontaneous reports of fatal GI events are in the geriatric population [see Warnings and Precautions (5.4)].

Naproxen is known to be substantially excreted by the kidney, and the risk of toxic reactions to this drug may be greater in patients with impaired renal function. Because elderly patients are more likely to have decreased renal function, care should be taken in dose selection, and it may be useful to monitor renal function. Geriatric patients may be at a greater risk for the development of a form of renal toxicity precipitated by reduced prostaglandin formation during administration of NSAIDs [see Warnings and Precautions (5.6, 5.7)].

8.6 Hepatic Insufficiency

VIMOVO should be avoided in patients with severe hepatic impairment because naproxen may increase the risk of renal failure or bleeding and esomeprazole doses should not exceed 20 mg daily in these patients [see Dosage and Administration (2), Warnings and Precautions (5.11) and Clinical Pharmacology (12.3)].

8.7 Renal Insufficiency

Naproxen-containing products, including VIMOVO, are not recommended for use in patients with advanced renal disease [see Dosage and Administration (2), and Warnings and Precautions (5.6, 5.7)].

10 OVERDOSAGE

There is no clinical data on overdosage with VIMOVO.

Overdosage of naproxen:

Significant naproxen overdosage may be characterized by lethargy, dizziness, drowsiness, epigastric pain, abdominal discomfort, heartburn, indigestion, nausea, transient alterations in liver function, hypoprothrombinemia, renal dysfunction, metabolic acidosis, apnea, disorientation or vomiting. Gastrointestinal bleeding can occur. Hypertension, acute renal failure, respiratory depression, and coma may occur, but are rare. Anaphylactoid reactions have been reported with therapeutic ingestion of NSAIDs, and may occur following an overdose. A few patients have experienced convulsions, but it is not clear whether or not these were drug-related. It is not known what dose of the drug would be life threatening. The oral LD50 of the drug is 543 mg/kg in rats, 1234 mg/kg in mice, 4110 mg/kg in hamsters, and greater than 1000 mg/kg in dogs.

Patients should be managed by symptomatic and supportive care following an NSAID overdose. There are no specific antidotes. Hemodialysis does not decrease the plasma concentration of naproxen because of the high degree of its protein binding. Activated charcoal (60 to 100 g in adults, 1 to 2 g/kg in children) and/or osmotic cathartic may be indicated in patients seen within 4 hours of ingestion with symptoms or following a large overdose. Forced diuresis, alkalinization of urine or hemoperfusion may not be useful due to high protein binding.

Overdosage of esomeprazole:

A single oral dose of esomeprazole at 510 mg/kg (about 103 times the human dose on a body surface area basis) was lethal to rats. The major signs of acute toxicity were reduced motor activity, changes in respiratory frequency, tremor, ataxia, and intermittent clonic convulsions.

The symptoms described in connection with deliberate esomeprazole overdose (limited experience of doses in excess of 240 mg/day) are transient. Single doses of 80 mg of esomeprazole were uneventful. Reports of overdosage with omeprazole in humans may also be relevant. Doses ranged up to 2,400 mg (120 times the usual recommended clinical dose). Manifestations were variable, but included confusion, drowsiness, blurred vision, tachycardia, nausea, diaphoresis, flushing, headache, dry mouth, and other adverse reactions similar to those seen in normal clinical experience (see omeprazole package insert - Adverse Reactions). No specific antidote for esomeprazole is known. Since esomeprazole is extensively protein bound, it is not expected to be removed by dialysis. In the event of overdosage, treatment should be symptomatic and supportive.

If overexposure occurs, call the Poison Control Center at 1- 800-222-1222.

11 DESCRIPTION

The active ingredients of VIMOVO are naproxen which is a NSAID and esomeprazole magnesium which is a Proton Pump Inhibitor (PPI).

VIMOVO is available as an oval, yellow, multi-layer, delayed release tablet combining an enteric coated naproxen core and an immediate release esomeprazole magnesium layer surrounding the core. Each strength contains either 375 mg of naproxen and 20 mg of esomeprazole (present as 22.3 mg esomeprazole magnesium trihydrate) or 500 mg of naproxen and 20 mg of esomeprazole (present as 22.3 mg esomeprazole magnesium trihydrate) for oral administration. The inactive ingredients are carnauba wax, colloidal silicon dioxide, croscarmellose sodium, iron oxide yellow, glyceryl monostearate, hypromellose, iron oxide black, magnesium stearate, methacrylic acid copolymer dispersion, methylparaben, polysorbate 80, polydextrose, polyethylene glycol, povidone, propylene glycol, propylparaben, titanium dioxide, and triethyl citrate.

The chemical name for naproxen is (S)-6-methoxy-α-methyl- 2-naphthaleneacetic acid. Naproxen has the following structure:

Naproxen has a molecular weight of 230.26 and a molecular formula of C14H14O3.

Naproxen is an odorless, white to off-white crystalline substance. It is lipid soluble, practically insoluble in water at low pH and freely soluble in water at high pH. The octanol/water partition coefficient of naproxen at pH 7.4 is 1.6 to 1.8.

The chemical name for esomeprazole is bis(5-methoxy-2- [(S)-[(4-methoxy-3,5-dimethyl-2-pyridinyl)methyl]sulfinyl]-1H-benzimidazole-1-yl) magnesium trihydrate. Esomeprazole is the S-isomer of omeprazole, which is a mixture of the S- and R-isomers. Its molecular formula is (C17H18N3O3S)2Mg x 3 H2O with molecular weight of 767.2 as a trihydrate and 713.1 on an anhydrous basis. The structural formula is:

The magnesium salt is a white to slightly colored crystalline powder. It contains 3 moles of water of solvation and is slightly soluble in water.

The stability of esomeprazole magnesium is a function of pH; it rapidly degrades in acidic media, but it has acceptable stability under alkaline conditions. At pH 6.8 (buffer), the half-life of the magnesium salt is about 19 hours at 25°C and about 8 hours at 37°C.

12 CLINICAL PHARMACOLOGY

12.1 Mechanism of Action

VIMOVO consists of an immediate-release esomeprazole magnesium layer and an enteric-coated naproxen core. As a result, esomeprazole is released first in the stomach, prior to the dissolution of naproxen in the small intestine. The enteric coating prevents naproxen release at pH levels below 5.5.

Naproxen is a NSAID with analgesic and antipyretic properties. The mechanism of action of the naproxen anion, like that of other NSAIDs, is not completely understood but may be related to prostaglandin synthetase inhibition.

Esomeprazole is a proton pump inhibitor that suppresses gastric acid secretion by specific inhibition of the H^+/K^+-ATPase in the gastric parietal cell. Esomeprazole is protonated and converted in the acidic compartment of the parietal cell forming the active inhibitor, the achiral sulphenamide. By acting specifically on the proton pump, esomeprazole blocks the final step in acid production, thus reducing gastric acidity. This effect is dose-related up to a daily dose of 20 to 40 mg and leads to inhibition of gastric acid secretion.

12.2 Pharmacodynamics

Antisecretory Activity

The effect of VIMOVO on intragastric pH was determined in 25 healthy volunteers in one study. Three VIMOVO combinations (naproxen 500 mg combined with either esomeprazole 10, 20, or 30 mg) were administered twice daily over 9 days. The results are shown in the following table:

Table 3: Effect on Intragastric pH on Day 9 (N=25)
 | Naproxen 500 mg combined with esomeprazole
 | 10 mg | 20 mg | 30 mg
% Time Gastric pH >4 | 41.1 (3.0) | 71.5 (3.0) | 76.8 (3.0)
Coefficient of variation | 55% | 18% | 16%

Serum Gastrin Effects

The effect of esomeprazole on serum gastrin concentrations was evaluated in approximately 2,700 patients in clinical trials up to 8 weeks and in over 1,300 patients for up to 6-12 months. The mean fasting gastrin level increased in a dose-related manner. This increase reached a plateau within two to three months of therapy and returned to baseline levels within four weeks after discontinuation of therapy.

Increased gastrin causes enterochromaffin-like cell hyperplasia and increased serum Chromogranin A (CgA) levels. The increased CgA levels may cause false positive results in diagnostic investigations for neuroendocrine tumors.

Enterochromaffin-like (ECL) Cell Effects

In over 1,000 patients treated with esomeprazole (10, 20 or 40 mg/day) up to 6-12 months, the prevalence of ECL cell hyperplasia increased with time and dose. No patient developed ECL cell carcinoids, dysplasia, or neoplasia in the gastric mucosa.

Endocrine Effects

Esomeprazole had no effect on thyroid function when given in oral doses of 20 or 40 mg for 4 weeks. Other effects of esomeprazole on the endocrine system were assessed using omeprazole studies. Omeprazole given in oral doses of 30 or 40 mg for 2 to 4 weeks had no effect on carbohydrate metabolism, circulating levels of parathyroid hormone, cortisol, estradiol, testosterone, prolactin, cholecystokinin or secretin.

Effects on Gastrointestinal Microbial Ecology

Decreased gastric acidity due to any means including proton pump inhibitors, increases gastric counts of bacteria normally present in the gastrointestinal tract. Treatment with proton pump inhibitors may lead to slightly increased risk of gastrointestinal infections such as Salmonella and Campylobacter and possibly Clostridium difficile in hospitalized patients.

12.3 Pharmacokinetics

Absorption

Naproxen

At steady state following administration of VIMOVO twice daily, peak plasma concentrations of naproxen are reached on average 3 hours following both the morning and the evening dose.

Bioequivalence between VIMOVO and enteric-coated naproxen, based on both area under the plasma concentration-time curve (AUC) and maximum plasma concentration (Cmax) of naproxen, has been demonstrated for both the 375 mg and 500 mg doses.

Naproxen is absorbed from the gastrointestinal tract with an in vivo bioavailability of 95%.

Steady-state levels of naproxen are reached in 4 to 5 days.

Esomeprazole

Following administration of VIMOVO twice daily, esomeprazole is rapidly absorbed with peak plasma concentration reached within on average, 0.43 to 1.2 hours, following the morning and evening dose on both the first day of administration and at steady state. The peak plasma concentrations of esomeprazole are higher at steady state compared to on first day of dosing of VIMOVO.

Figure 1 represents the pharmacokinetics of naproxen and esomeprazole following administration of VIMOVO 500 mg/20 mg.

Figure 1: Mean plasma concentrations of naproxen and esomeprazole following single dose administration of VIMOVO (500mg/20 mg)

Food effect

Administration of VIMOVO together with high-fat food in healthy volunteers does not affect the extent of absorption of naproxen but significantly prolongs tmax by 10 hours and decreases peak plasma concentration (Cmax) by about 12%.

Administration of VIMOVO together with high-fat food in healthy volunteers delays tmax of esomeprazole by 1 hour and significantly reduces the extent of absorption, resulting in 52% and 75% reductions of area under the plasma concentration versus time curve (AUC) and peak plasma concentration (Cmax), respectively.

Administration of VIMOVO 30 minutes before high-fat food intake in healthy volunteers does not affect the extent of absorption of naproxen but delays the absorption by about 4 hours and decreases peak plasma concentration (Cmax) by about 17%, but has no significant effect on the rate or extent of esomeprazole absorption compared to administration under fasted conditions [see Dosage and Administration (2)].

Administration of VIMOVO 60 minutes before high-fat food intake in healthy volunteers has no effect on the rate and extent of naproxen absorption; however, increases the esomeprazole AUC by 25% and Cmax by 50% compared to administration under fasted conditions. This increase in esomeprazole Cmax does not raise a safety issue since the approved dosing regimen of esomeprazole at 40 mg QD would result in higher Cmax [see Dosage and Administration (2)].

Therefore, VIMOVO should be taken at least 30 minutes before the meal.

Distribution

Naproxen

Naproxen has a volume of distribution of 0.16 L/kg. At therapeutic levels naproxen is greater than 99% albumin-bound. At doses of naproxen greater than 500 mg/day there is less than proportional increase in plasma levels due to an increase in clearance caused by saturation of plasma protein binding at higher doses (average trough Css 36.5, 49.2 and 56.4 mg/L with 500, 1000 and 1500 mg daily doses of naproxen, respectively). The naproxen anion has been found in the milk of lactating women at a concentration equivalent to approximately 1% of maximum naproxen concentration in plasma [see Use in Specific Populations (8.3)].

Esomeprazole

The apparent volume of distribution at steady state in healthy subjects is approximately 16L. Esomeprazole is 97% plasma protein bound.

Metabolism

Naproxen

Naproxen is extensively metabolized in the liver by the cytochrome P450 system (CYP), CYP2C9 and CYP1A2, to 6-0-desmethyl naproxen. Neither the parent drug nor the metabolites induce metabolizing enzymes. Both naproxen and 6-0-desmethyl naproxen are further metabolized to their respective acylglucuronide conjugated metabolites. Consistent with the half-life of naproxen, the area under the plasma concentration time curve increases with repeated dosing of VIMOVO twice daily.

Esomeprazole

Esomeprazole is extensively metabolized in the liver by the CYP enzyme system. The major part of the metabolism of esomeprazole is dependent on the polymorphic CYP2C19, responsible for the formation of the hydroxyl- and desmethyl metabolites of esomeprazole. The remaining part is dependent on another specific isoform CYP3A4, responsible for the formation of esomeprazole sulphone, the main metabolite in plasma. The major metabolites of esomeprazole have no effect on gastric acid secretion.

The area under the plasma esomeprazole concentration-time curve increases with repeated administration of VIMOVO. This increase is dose-dependent and results in a non-linear dose-AUC relationship after repeated administration. An increased absorption of esomeprazole with repeated administration of VIMOVO probably also contributes to the time-and dose-dependency.

Excretion

Naproxen

Following administration of VIMOVO twice daily, the mean elimination half-life for naproxen is approximately 15 hours following the evening dose, with no change with repeated dosing.

The clearance of naproxen is 0.13 mL/min/kg. Approximately 95% of the naproxen from any dose is excreted in the urine, primarily as naproxen (<1%), 6-0-desmethyl naproxen (<1%) or their conjugates (66% to 92%). Small amounts, 3% or less of the administered dose, are excreted in the feces. In patients with renal failure, metabolites may accumulate [see Warnings and Precautions (5.6, 5.7)].

Esomeprazole

Following administration of VIMOVO twice daily, the mean elimination half-life of esomeprazole is approximately 1 hour following both the morning and evening dose on day 1, with a slightly longer elimination half-life at steady state (1.2-1.5 hours).

Almost 80% of an oral dose of esomeprazole is excreted as metabolites in the urine, the remainder in the feces. Less than 1% of the parent drug is found in the urine.

Special Populations

Geriatric Patients

There is no specific data on the pharmacokinetics of VIMOVO in patients over age 65.

Studies indicate that although total plasma concentration of naproxen is unchanged, the unbound plasma fraction of naproxen is increased in the elderly, although the unbound fraction is <1% of the total naproxen concentration. Unbound trough naproxen concentrations in elderly subjects have been reported to range from 0.12% to 0.19% of total naproxen concentration, compared with 0.05% to 0.075% in younger subjects. The clinical significance of this finding is unclear, although it is possible that the increase in free naproxen concentration could be associated with an increase in the rate of adverse events per a given dosage in some elderly patients [see Adverse Reactions (6) and Use in Specific Populations (8.5)].

The AUC and Cmax values of esomeprazole were slightly higher (25% and 18%, respectively) in the elderly as compared to younger subjects at steady state. Dosage adjustment for the esomeprazole component based on age is not necessary.

Race

Pharmacokinetic differences due to race have not been studied for naproxen.

Approximately 3% of Caucasians and 15 to 20% of Asians lack a functional CYP2C19 enzyme and are called poor metabolizers. In these individuals the metabolism of esomeprazole is probably mainly catalyzed by CYP3A4. After repeated once-daily administration of 40 mg esomeprazole, the mean area under the plasma concentration-time curve was approximately 100% higher in poor metabolizers than in subjects having a functional CYP2C19 enzyme (extensive metabolizers).

Hepatic Insufficiency

The pharmacokinetics of VIMOVO or naproxen have not been determined in subjects with hepatic impairment.

In patients with severe hepatic impairment, VIMOVO should be avoided due to increase of risk of NSAID associated bleeding and/or renal failure associated with naproxen.

Chronic alcoholic liver disease and probably also other forms of cirrhosis reduce the total plasma concentration of naproxen, but the plasma concentration of unbound naproxen is increased. The implication of this finding for the naproxen component of VIMOVO dosing is unknown but it is prudent to use the lowest effective dose.

The AUCs of esomeprazole in patients with severe hepatic insufficiency (Child Pugh Class C) have been shown to be 2-3 times higher than in patients with normal liver function. For this reason, it has been recommended that esomeprazole doses not exceed 20 mg daily in patients with severe hepatic impairment. However, there is no dose adjustment necessary for patients with Child Pugh Class A and B for the esomeprazole component of VIMOVO. There is no VIMOVO dosage form that contains less than 20 mg esomeprazole for twice daily dosing [see Dosage and Administration (2), Warnings and Precautions (5.11), and Use in Specific Populations (8.6)].

Renal Insufficiency

The pharmacokinetics of VIMOVO or naproxen have not been determined in subjects with renal impairment.

Given that naproxen, its metabolites and conjugates are primarily excreted by the kidney, the potential exists for naproxen metabolites to accumulate in the presence of renal insufficiency. Elimination of naproxen is decreased in patients with severe renal impairment. Naproxen-containing products, including VIMOVO, is not recommended for use in patients with moderate to severe and severe renal impairment (creatinine clearance <30 ml/min) [see Dosage and Administration (2), Warnings and Precautions (5.6, 5.7), and Use in Specific Populations (8.7)].

No studies have been performed with esomeprazole in patients with decreased renal function. Since the kidney is responsible for the excretion of the metabolites of esomeprazole but not for the elimination of the parent compound, the metabolism of esomeprazole is not expected to be changed in patients with impaired renal function.

Gender

The AUC and Cmax values of esomeprazole were slightly higher (13%) in females than in males at steady state. Dosage adjustment for the esomeprazole component based on gender is not necessary.

13 NONCLINICAL TOXICOLOGY

13.1 Carcinogenesis, Mutagenesis, Impairment of Fertility

Naproxen

A 2-year study was performed in rats to evaluate the carcinogenic potential of naproxen at rat doses of 8, 16, and 24 mg/kg/day (50, 100, and 150 mg/m^2). The maximum dose used was 0.28 times the highest recommended human dose. No evidence of tumorigenicity was found.

Esomeprazole

The carcinogenic potential of esomeprazole was assessed using omeprazole studies. In two 24-month oral carcinogenicity studies in rats, omeprazole at daily doses of 1.7, 3.4, 13.8, 44 and 140.8 mg/kg/day (about 0.7 to 57 times the human dose of 20 mg/day expressed on a body surface area basis) produced gastric ECL cell carcinoids in a dose-related manner in both male and female rats; the incidence of this effect was markedly higher in female rats, which had higher blood levels of omeprazole. Gastric carcinoids seldom occur in the untreated rat. In addition, ECL cell hyperplasia was present in all treated groups of both sexes. In one of these studies, female rats were treated with 13.8 mg omeprazole/kg/day (about 5.6 times the human dose on a body surface area basis) for 1 year, then followed for an additional year without the drug. No carcinoids were seen in these rats. An increased incidence of treatment-related ECL cell hyperplasia was observed at the end of 1 year (94% treated vs 10% controls). By the second year the difference between treated and control rats was much smaller (46% vs 26%) but still showed more hyperplasia in the treated group. Gastric adenocarcinoma was seen in one rat (2%). No similar tumor was seen in male or female rats treated for 2 years. For this strain of rat no similar tumor has been noted historically, but a finding involving only one tumor is difficult to interpret. A 78-week mouse carcinogenicity study of omeprazole did not show increased tumor occurrence, but the study was not conclusive.

Esomeprazole was negative in the Ames mutation test, in the in vivo rat bone marrow cell chromosome aberration test, and the in vivo mouse micronucleus test. Esomeprazole, however, was positive in the in vitro human lymphocyte chromosome aberration test. Omeprazole was positive in the in vitro human lymphocyte chromosome aberration test, the in vivo mouse bone marrow cell chromosome aberration test, and the in vivo mouse micronucleus test.

The potential effects of esomeprazole on fertility and reproductive performance were assessed using omeprazole studies. Omeprazole at oral doses up to 138 mg/kg/day in rats (about 56 times the human dose on a body surface area basis) was found to have no effect on reproductive performance of parental animals.

13.2 Animal Toxicology and/or Pharmacology

Naproxen

Reproductive studies have been performed in rats at 20 mg/kg/day (125 mg/m^2/day, 0.23 times the maximum recommended human dose), rabbits at 20 mg/kg/day (220 mg/m^2/day, 0.27 times the maximum recommended human dose), and mice at 170 mg/kg/day (510 mg/m^2/day, 0.28 times the maximum recommended human dose) with no evidence of impaired fertility or harm to the fetus due to the drug. However, animal reproduction studies are not always predictive of human response.

Esomeprazole

Reproductive studies have been performed in rats at oral doses up to 280 mg/kg/day (about 57 times the human dose on a body surface area basis) and in rabbits at oral doses up to 86 mg/kg/day (about 35 times the human dose on a body surface area basis) and have revealed no evidence of impaired fertility or harm to the fetus due to esomeprazole.

Reproductive studies conducted with omeprazole in rats at oral doses up to 138 mg/kg/day (about 56 times the human dose on a body surface area basis) and in rabbits at doses up to 69 mg/kg/day (about 56 times the human dose on a body surface area basis) did not disclose any evidence for a teratogenic potential of omeprazole. In rabbits, omeprazole in a dose range of 6.9 to 69.1 mg/kg/day (about 5.5 to 56 times the human dose on a body surface area basis) produced dose-related increases in embryo-lethality, fetal resorptions, and pregnancy disruptions. In rats, dose-related embryo/fetal toxicity and postnatal developmental toxicity were observed in offspring resulting from parents treated with omeprazole at 13.8 to 138.0 mg/kg/day (about 5.6 to 56 times the human doses on a body surface area basis).

14 CLINICAL STUDIES

Two randomized, multi-center, double-blind trials (Study 1 and Study 2) compared the incidence of gastric ulcer formation in 428 patients taking VIMOVO and 426 patients taking enteric-coated naproxen. Subjects were at least 18 years of age with a medical condition expected to require daily NSAID therapy for at least 6 months, and, if less than 50 years old, with a documented history of gastric or duodenal ulcer within the past 5 years. The majority of patients were female (67%), white (86%). The majority of patients were 50-69 years of age (83%). Approximately one quarter were on low-dose aspirin.

Studies 1 and 2 showed that VIMOVO given as 500 mg/20 mg twice daily statistically significantly reduced the 6-month cumulative incidence of gastric ulcers compared to enteric-coated naproxen 500 mg twice daily (see Table 4).

Approximately a quarter of the patients in Studies 1 and 2 were taking concurrent low-dose aspirin (≤ 325 mg daily). The results for this subgroup analysis in patients who used aspirin were consistent with the overall findings of the study.

The results at one month, three months, and six months are presented in Table 4.

Table 4 – Cumulative Observed Incidence of Gastric Ulcers at 1, 3 and 6 Months
 | Study 1 |  | Study 2
 | VIMOVO; N=218 number (%) | EC-naproxen; N=216 number (%) | VIMOVO; N=210 number (%) | EC-naproxen; N=210 number (%)
0-1 Month | 3 (1.4) | 28 (13.0) | 4 (1.9) | 21 (10.0)
0-3 Months | 4 (1.8) | 42 (19.4) | 10 (4.8) | 37 (17.6)
0-6 Months | 9 (4.1) | 50 (23.1) | 15 (7.1) | 51 (24.3)

In these trials, patients receiving VIMOVO had a mean duration of therapy of 152 days compared to 124 days in patients receiving enteric-coated naproxen alone. A higher proportion of patients taking EC-naproxen (12%) discontinued the study due to upper GI adverse events (including duodenal ulcers) compared to VIMOVO (4%) in both trials [see Adverse Reactions (6)].

The efficacy of VIMOVO in treating the signs and symptoms of osteoarthritis was established in two 12-week randomized, double-blind, placebo-controlled trials in patients with osteoarthritis (OA) of the knee. In these two trials, patients were allowed to remain on low-dose aspirin for cardioprophylaxis. VIMOVO was given as 500 mg/20 mg twice daily. In each trial, patients receiving VIMOVO had significantly better results compared to patients receiving placebo as measured by change from baseline of the WOMAC pain subscale and the WOMAC physical function subscale and a Patient Global Assessment Score.

Based on studies with enteric-coated naproxen, improvement in patients treated for rheumatoid arthritis was demonstrated by a reduction in joint swelling, a reduction in duration of morning stiffness, a reduction in disease activity as assessed by both the investigator and patient, and by increased mobility as demonstrated by a reduction in walking time. In patients with osteoarthritis, the therapeutic action of naproxen has been shown by a reduction in joint pain or tenderness, an increase in range of motion in knee joints, increased mobility as demonstrated by a reduction in walking time, and improvement in capacity to perform activities of daily living impaired by the disease. In patients with ankylosing spondylitis, naproxen has been shown to decrease night pain, morning stiffness and pain at rest.

16 HOW SUPPLIED/STORAGE AND HANDLING

VIMOVO 375 mg/20 mg tablets are oval, yellow film-coated tablets printed with 375/20 in black ink, supplied as:

NDC 0186-0510-60 Bottles of 60 tablets

VIMOVO 500 mg/20 mg tablets are oval, yellow film-coated tablets printed with 500/20 in black ink, supplied as:

NDC 0186-0520-60 Bottles of 60 tablets

NDC 0186-0520-39 Unit Dose Blisters, package of 100 tablets

Storage: Store at 25°C (77°F); excursions permitted to 15- 30°C (59-86°F) [see USP Controlled Room Temperature]. Store in the original container and keep the bottle tightly closed to protect from moisture. Dispense in a tight container if package is subdivided.

17 PATIENT COUNSELING INFORMATION

[See Medication Guide]

Patients should be informed of the following before initiating therapy with VIMOVO and periodically during the course of ongoing therapy. Patients should also be encouraged to read the NSAID Medication Guide that accompanies each prescription dispensed.

1. VIMOVO, like other NSAID-containing products, may cause serious cardiovascular side effects, such as myocardial infarction or stroke, which may result in hospitalization and even death. Although serious cardiovascular events can occur without warning symptoms, patients should be alert for the signs and symptoms of chest pain, shortness of breath, weakness, slurring of speech, and should ask for medical advice when observing any indicative sign or symptoms. Patients should be apprised of the importance of this follow-up [see Warnings and Precautions (5.1)].

2. VIMOVO has been developed with esomeprazole to decrease incidence of ulceration from naproxen. NSAIDs, including naproxen, can cause GI discomfort and, rarely, serious GI side effects, such as ulcers and bleeding, which may result in hospitalization and even death. Although serious GI tract ulcerations and bleeding can occur without warning symptoms, patients should be alert for the signs and symptoms of ulcerations and bleeding, and should ask for medical advice when observing any indicative sign or symptoms including epigastric pain, dyspepsia, melena, and hematemesis. Patients should be apprised of the importance of this follow-up [see Warnings and Precautions (5.4)].

3. VIMOVO, like other NSAID-containing products, can cause serious skin side effects such as exfoliative dermatitis, Stevens-Johnson syndrome, and toxic epidermal necrolysis, which may result in hospitalizations and even death. Although serious skin reactions may occur without warning, patients should be alert for the signs and symptoms of skin rash and blisters, fever, or other signs of hypersensitivity such as itching, and should ask for medical advice when observing any indicative signs or symptoms. Patients should be advised to stop the drug immediately if they develop any type of rash and contact their physicians as soon as possible [see Warnings and Precautions (5.9)].

4. Patients should promptly report signs or symptoms of unexplained weight gain or edema to their physicians.

5. Patients should be informed of the warning signs and symptoms of hepatotoxicity (eg, nausea, fatigue, lethargy, pruritus, jaundice, right upper quadrant tenderness, and “flu-like” symptoms). If these occur, patients should be instructed to stop therapy and seek immediate medical therapy [see Contraindications (4) and Warnings and Precautions (5.11)].

6. Patients should be informed of the signs of an anaphylactoid reaction (eg, difficulty breathing, swelling of the face or throat). If these occur, patients should be instructed to seek immediate emergency help [see Warnings and Precautions (5.8)].

7. In late pregnancy, as with other NSAIDs, VIMOVO should be avoided because it may cause premature closure of the ductus arteriosus [see Contraindications (4), Warnings and Precautions (5.10) and Use in Specific Populations (8.1)].

8. Caution should be exercised by patients whose activities require alertness if they experience drowsiness, dizziness, vertigo or depression during therapy with VIMOVO.

9. Patients should be instructed to tell their physicians if they have a history of asthma or aspirin-sensitive asthma because the use of NSAIDs in patients with aspirin-sensitive asthma has been associated with severe bronchospasm, which can be fatal. Patients with this form of aspirin sensitivity should be instructed not to take VIMOVO. Patients with preexisting asthma should be instructed to seek immediate medical attention if their asthma worsens after taking VIMOVO [see Warnings and Precautions (5.8, 5.13)].

10. Antacids may be used while taking VIMOVO.

11. VIMOVO tablets should be swallowed whole with liquid. Tablets should not be split, chewed, crushed or dissolved. VIMOVO tablets should be taken at least 30 minutes before meals [see Dosage and Administration (2)].

12. Advise patients to immediately report and seek care for any cardiovascular or neurological symptoms including palpitations, dizziness, seizures, and tetany as these may be signs of hypomagnesemia [see Warnings and Precautions (5.19)].

VIMOVO is a trademark of the AstraZeneca group of companies. Other trademarks are the property of their respective companies.

Distributed by: AstraZeneca LP, Wilmington, DE 19850

©AstraZeneca 2011

MEDICATION GUIDE

VIMOVO (vi-moh´-voh)

(naproxen and esomeprazole magnesium)

Delayed Release Tablets

Read this Medication Guide before you start taking VIMOVO and each time you get a refill. There may be new information. This information does not take the place of talking with your healthcare provider about your medical condition or your treatment.

What is the most important information I should know about VIMOVO?

VIMOVO, which contains naproxen [a nonsteroidal anti-inflammatory drug (NSAID)] and esomeprazole magnesium, may increase the chance of a heart attack or stroke that can lead to death. This chance increases:

- with longer use of NSAID medicines
- in people who have heart disease

NSAID-containing medicines, such as VIMOVO, should never be used right before or after a heart surgery called a coronary artery bypass graft (CABG).

NSAID-containing medicines, such as VIMOVO, can cause ulcers and bleeding in the stomach and intestines at any time during treatment. Ulcers and bleeding:

- can happen without warning symptoms
- may cause death

The chance of a person getting an ulcer or bleeding increases with:

- taking medicines called steroid hormones (corticosteroids) and blood thinners (anticoagulants)
- longer use
- smoking
- drinking alcohol
- older age
- having poor health

NSAID medicines should only be used:

- exactly as prescribed
- at the lowest dose possible for your treatment
- for the shortest time needed

What are Non-Steroidal Anti-Inflammatory Drugs (NSAIDs)?

NSAID medicines are used to treat pain and redness, swelling, and heat (inflammation) from medical conditions such as:

- different types of arthritis
- menstrual cramps and other types of short-term pain

Who should not take a Non–Steroidal Anti–Inflammatory Drug (NSAID)?

Do not take an NSAID medicine:

- if you had an asthma attack, hives, or other allergic reaction with aspirin or any other NSAID medicine
- for pain right before or after heart bypass surgery

Tell your healthcare provider:

- about all of your medical conditions
- about all of the medicines you take. NSAIDs and some other medicines can interact with each other and cause serious side effects. Keep a list of your medicines to show to your healthcare provider and pharmacist.
- if you are pregnant. NSAID medicines should not be used by pregnant women late in their pregnancy.
- if you are breastfeeding. Talk to your healthcare provider.

What are the possible side effects of Non–Steroidal Anti–Inflammatory Drugs (NSAIDs)?

Serious side effects include:

heart attack

stroke

high blood pressure

heart failure from body swelling (fluid retention)

kidney problems including kidney failure

bleeding and ulcers in the stomach and intestine

low red blood cells (anemia)

life-threatening skin reactions

life-threatening allergic reactions

liver problems including liver failure

asthma attacks in people who have asthma

Other side effects include:

stomach pain

constipation

diarrhea

gas

heartburn

nausea

vomiting

dizziness

Get emergency help right away if you have any of the following symptoms:

- shortness of breath or trouble breathing
- chest pain
- weakness in one part or side of your body
- slurred speech
- swelling of the face or throat

Stop your NSAID medicine and call your healthcare provider right away if you have any of the following symptoms:

- nausea
- more tired or weaker than usual
- itching
- your skin or eyes look yellow
- stomach pain
- flu-like symptoms
- vomit blood
- there is blood in your bowel movement or it is black and sticky like tar
- skin rash or blisters with fever
- unusual weight gain
- swelling of the arms and legs, hands and feet

These are not all of the possible side effects with NSAID medicines. Talk to your healthcare provider or pharmacist for more information about NSAID medicines. Call your healthcare provider for medical advice about side effects. You may report side effects to FDA at 1-800-FDA-1088.

Other information about Non–Steroidal Anti–Inflammatory Drugs (NSAIDs)

- Aspirin is an NSAID medicine but it does not increase the chance of a heart attack. Aspirin can cause bleeding in the brain, stomach, and intestines. Aspirin can also cause ulcers in the stomach and intestines.
- Some of these NSAID medicines are sold in lower doses without a prescription (over-the-counter). Talk to your healthcare provider before using over-the-counter NSAIDs for more than 10 days.

NSAID medicines that need a prescription

Generic Name | TRADENAME
Celecoxib | Celebrex
Diclofenac | Cataflam, Voltaren, Arthrotec (combined with misoprostol) Voltaren
Diflunisal | Dolobid
Etodolac | Lodine, Lodine XL
Fenoprofen | Nalfon, Nalfon 200
Flurbiprofen | Ansaid
Ibuprofen | Motrin, Tab-Profen, Vicoprofen (combined with hydrocodone), Combunox (combined with oxycodone)
Indomethacin | Indocin, Indocin SR, Indo-Lemmon, Indomethagan
Ketoprofen | Oruvail
Ketorolac | Toradol
Mefenamic Acid | Ponstel
Meloxicam | Mobic
Nabumetone | Relafen
Naproxen | Naprosyn, Anaprox, Anaprox DS, EC-Naprosyn, Naprelan, VIMOVO
Oxaprozin | Daypro
Piroxicam | Feldene
Sulindac | Clinoril
Tolmetin | Tolectin, Tolectin DS, Tolectin 600

What is VIMOVO?

VIMOVO contains 2 medicines: naproxen, a non-steroidal anti-inflammatory drug (NSAID) and esomeprazole magnesium, a proton pump inhibitor (PPI).

VIMOVO is a prescription medicine used to:

- relieve signs and symptoms of osteoarthritis, rheumatoid arthritis, and ankylosing spondylitis
- decrease the risk of developing stomach (gastric) ulcers in people who are at risk of developing gastric ulcers with NSAIDs

It is not known if VIMOVO is safe or effective in children under the age of 18.

Who should not take VIMOVO?

Do not take VIMOVO:

- If you had an asthma attack, hives, or other allergic reaction after taking aspirin or other NSAID medicine.
- If you are allergic to any of the ingredients in VIMOVO. See the end of this leaflet for a complete list of ingredients in VIMOVO.
- If you are allergic to any other Proton Pump Inhibitor (PPI) medicine.
- For pain right before or after heart bypass surgery
- If you are in the late stages of pregnancy (third trimester)

What should I tell my healthcare provider before taking VIMOVO?

Before you take VIMOVO, tell your healthcare provider about all your medical conditions, including if you:

- have been told that you have low magnesium levels in your blood
- have liver or kidney problems
- have ulcerative colitis or Crohn’s disease (inflammatory bowel disease or IBD)
- have any other medical conditions
- are pregnant or plan to become pregnant. See “What is the most important information I should know about VIMOVO?”
- are breast-feeding or plan to breast-feed. VIMOVO can pass into your milk and may harm your baby. You should not breast-feed while taking VIMOVO. Talk to your healthcare provider about the best way to feed your baby if you take VIMOVO.

Tell your healthcare provider about all the medicines you take, including prescription and non-prescription medicines, vitamins, and herbal supplements. Since VIMOVO contains naproxen, talk to your healthcare provider before taking any other NSAID-containing products.

Especially tell your healthcare provider if you take:

- steroid hormones (corticosteroids)
- St. John's Wort
- rifampin (Rifater, Rifamate, Rimactane, Rifadin)
- a medicine for high blood pressure or heart problems
- aspirin
- cholestyramine (Questran, Questran Light, Locholest, Locholest Light, Prevalite)
- cyclosporine (Gengraf, Neoral, Sandimmune) or tacrolimus (Prograf)
- a water pill (diuretic)
- lithium carbonate
- methotrexate sodium (Trexall)
- blood thinner medicines, including warfarin sodium (Coumadin, Jantoven), dicumarol, or a blood thinner that contains heparin
- an antidepressant medicine

Ask your healthcare provider if you are not sure if your medicine is one that is listed above.

Using VIMOVO with other medicines can cause serious side effects. VIMOVO may affect the way other medicines work, and other medicines may affect how VIMOVO works.

Know the medicines you take. Keep a list of them to show your healthcare provider or pharmacist when you get a new medicine.

How should I take VIMOVO?

- Take VIMOVO exactly as your healthcare provider tells you to take it.
- Your healthcare provider may tell you to take Vitamin D and Calcium supplements during treatment with VIMOVO.
- Your healthcare provider will tell you how many VIMOVO to take and when to take them.
- Do not change your dose or stop VIMOVO without first talking to your healthcare provider.
- Take VIMOVO at least 30 minutes before a meal.
- Swallow VIMOVO tablets whole with liquid. Do not split, chew, crush or dissolve the VIMOVO tablet. Tell your healthcare provider if you cannot swallow the tablet whole. You may need a different medicine.
- You may use antacids while taking VIMOVO.
- If you forget to take a dose of VIMOVO, take it as soon as you remember. If it is almost time for your next dose, do not take the missed dose. Take the next dose on time. Do not take 2 doses at one time to make up for a missed dose.
- If you take too much VIMOVO, tell your healthcare provider or go to the closest hospital emergency room right away. Symptoms that you have taken too much VIMOVO may include:
  - feeling weak and tired
  - dizziness
  - feeling sleepy
  - upper stomach-area pain or discomfort
  - heartburn, indigestion, or nausea
  - a change in breathing or you stop breathing
  - vomiting
  - bleeding
  - movements of a body part that you cannot control
  - coordination problems and decreased movement

If you take more VIMOVO than your healthcare provider recommends, call your Poison Control Center at 1-800-222-1222.

- Your healthcare provider may do certain tests from time to time to check you for side effect of VIMOVO.

What should I avoid while taking VIMOVO?

VIMOVO can cause drowsiness, dizziness, or depression. You should not drive or do other activities that require you to be alert until you know how VIMOVO affects you.

What are the possible side effects of VIMOVO?

VIMOVO may cause serious side effects.

See “What is the most important information I should know about VIMOVO?”

- High blood pressure.
- Heart problems such as congestive heart failure. Tell your healthcare provider about any swelling of your body, hands or feet, sudden weight gain or trouble breathing.
- Active bleeding. Tell your healthcare provider if you have signs of active bleeding including:
  - passing black sticky bowel movements (stools)
  - having bloody diarrhea
  - vomiting or coughing up blood or dark particles that look like coffee grounds
- Serious allergic reactions. Tell your healthcare provider or get medical help right away if you develop sudden wheezing, swelling of your lips, tongue, throat or body, rash, fainting or problems breathing or swallowing (severe allergic reaction).
- Serious skin reactions. Tell your healthcare provider or get medical help right away if you develop:
  - reddening of your skin with blisters or peeling
  - blisters and bleeding of your lips, eye lids, mouth, nose, and genitals.
- Liver problems. Tell your healthcare provider if you develop:
  - yellowing of the skin or the whites of your eyes
  - dark urine
  - feel tired
  - nausea
  - right upper stomach area (abdomen) pain
  - flu-like symptoms
- Bone Fracture. Talk to your healthcare provider about your risk for fractures if you take VIMOVO for a long period of time.
- Low magnesium levels in your body. This problem can be serious. Low magnesium can happen in some people who take a proton pump inhibitor medicine for at least 3 months. If low magnesium levels happen, it is usually after a year of treatment. You may or may not have symptoms of low magnesium.

Tell your doctor right away if you have any of these symptoms:

- seizures
- dizziness
- abnormal or fast heart beat
- jitteriness
- jerking movements or shaking (tremors)
- muscle weakness
- spasms of the hands and feet
- cramps or muscle aches
- spasm of the voice box

Your doctor may check the level of magnesium in your body before you start taking VIMOVO, during treatment, or if you will be taking VIMOVO for a long period of time.

The most common side effects of VIMOVO include

- inflammation of the lining of the stomach, with or without loss of the protective layer of the stomach (erosive gastritis)
- indigestion
- diarrhea
- stomach ulcers
- upper stomach-area (abdominal) pain
- nausea

Tell your healthcare provider if you have any side effect that bothers you or that does not go away.

These are not all the possible side effects of VIMOVO. For more information, ask your healthcare provider or pharmacist.

Call your doctor for medical advice about side effects. You may report side effects to FDA at 1-800-FDA-1088.

How should I store VIMOVO?

- Store VIMOVO at 59°F to 86°F (15°C to 30°C)
- Keep VIMOVO in the original container and keep the bottle tightly closed.
- Keep VIMOVO dry.

Keep VIMOVO and all medicines out of the reach of children.

General information about VIMOVO

Medicines are sometimes prescribed for purposes other than those listed in this Medication Guide. Do not use VIMOVO for a condition for which it was not prescribed. Do not give VIMOVO to other people, even if they have the same symptoms you have. It may harm them.

This Medication Guide summarizes the most important information about VIMOVO. If you would like more information, ask your healthcare provider. You can ask your healthcare provider or pharmacist for information that is written for healthcare professionals.

For more information, call 1-800-236-9933 or go to www.VIMOVO.com

What are the ingredients in VIMOVO?

Active ingredients: naproxen and esomeprazole magnesium

Inactive ingredients: carnauba wax, colloidal silicon dioxide, croscarmellose sodium, iron oxide yellow, glyceryl monostearate, hypromellose, iron oxide black, magnesium stearate, methacrylic acid copolymer dispersion, methylparaben, polysorbate 80, polydextrose, polyethylene glycol, povidone, propylene glycol, propylparaben, titanium dioxide, and triethyl citrate.

Distributed by: AstraZeneca LP, Wilmington, DE 19850

Issued June 2011

This Medication Guide has been approved by the U.S. Food and Drug Administration.

VIMOVO is a trademark of the AstraZeneca group of companies.

Other trademarks are the property of their respective companies.